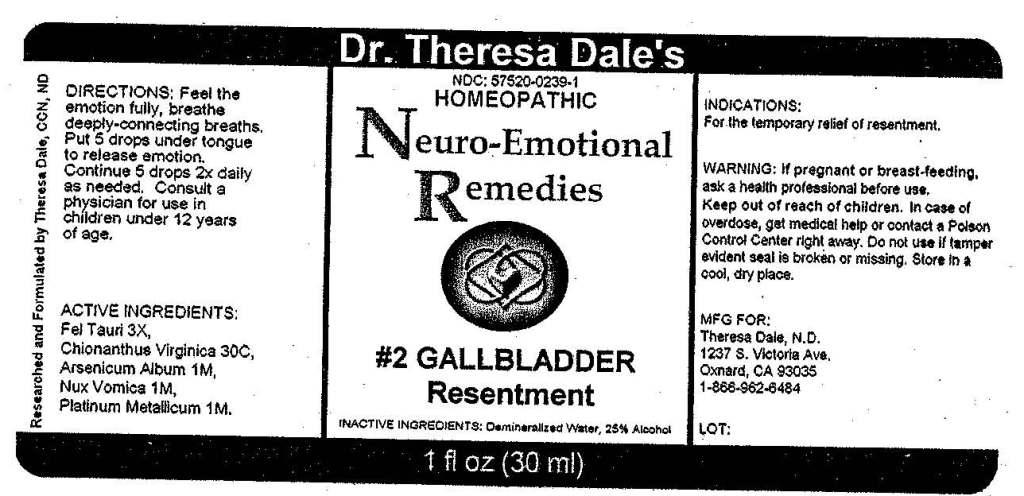 DRUG LABEL: 2 Gallbladder
NDC: 57520-0239 | Form: LIQUID
Manufacturer: Apotheca Company
Category: homeopathic | Type: HUMAN OTC DRUG LABEL
Date: 20100802

ACTIVE INGREDIENTS: CHIONANTHUS VIRGINICUS BARK 30 [hp_C]/1 mL; ARSENIC TRIOXIDE 1 [hp_M]/1 mL; STRYCHNOS NUX-VOMICA SEED 1 [hp_M]/1 mL; PLATINUM 1 [hp_M]/1 mL; BOS TAURUS BILE 3 [hp_X]/1 mL
INACTIVE INGREDIENTS: WATER; ALCOHOL

#2 Gallbladder

ACTIVE INGREDIENT

ACTIVE INGREDIENTS: Fel tauri 3X, Chionanthus virginica 30C, Arsenicum album 1M, Nux vomica 1M, Platinum metallicum 1M.

PURPOSE

INDICATIONS: For the temporary relief of resentment.

WARNINGS

WARNINGS: If pregnant or breast-feeding, ask a health professional before use.

Keep out of reach of children. In case of overdose, get medical help or contact a Poison Control Center right away.

Do not use if tamper evident seal is broken or missing. Store in a cool, dry place.

DOSAGE AND ADMINISTRATION

DIRECTIONS: Feel the emotion fully, breathe deeply-connecting breaths. Put 5 drops under tongue to release emotion. Continue 5 drops 2x daily as needed. Consult a physician for use in children under 12 years of age.

INACTIVE INGREDIENTS: Demineralized water, 25% Alcohol.

KEEP OUT OF REACH OF CHILDREN. In case of overdose, get medical help or contact a Poison Control Center right away.

INDICATIONS: For the temporary relief of resentment.

QUESTIONS

MFG. FOR:

Theresa Dale, N.D.

1237 S Victoria Ave.

Oxnard, CA 93035

1-866-962-6484

PACKAGE LABEL

Dr. Theresa Dale's

NDC: 57520-0239-1

HOMEOPATHIC

Neuro-Emotional Remedies

2 GALLBLADDER

Resentment

1 fl oz (30 ml)